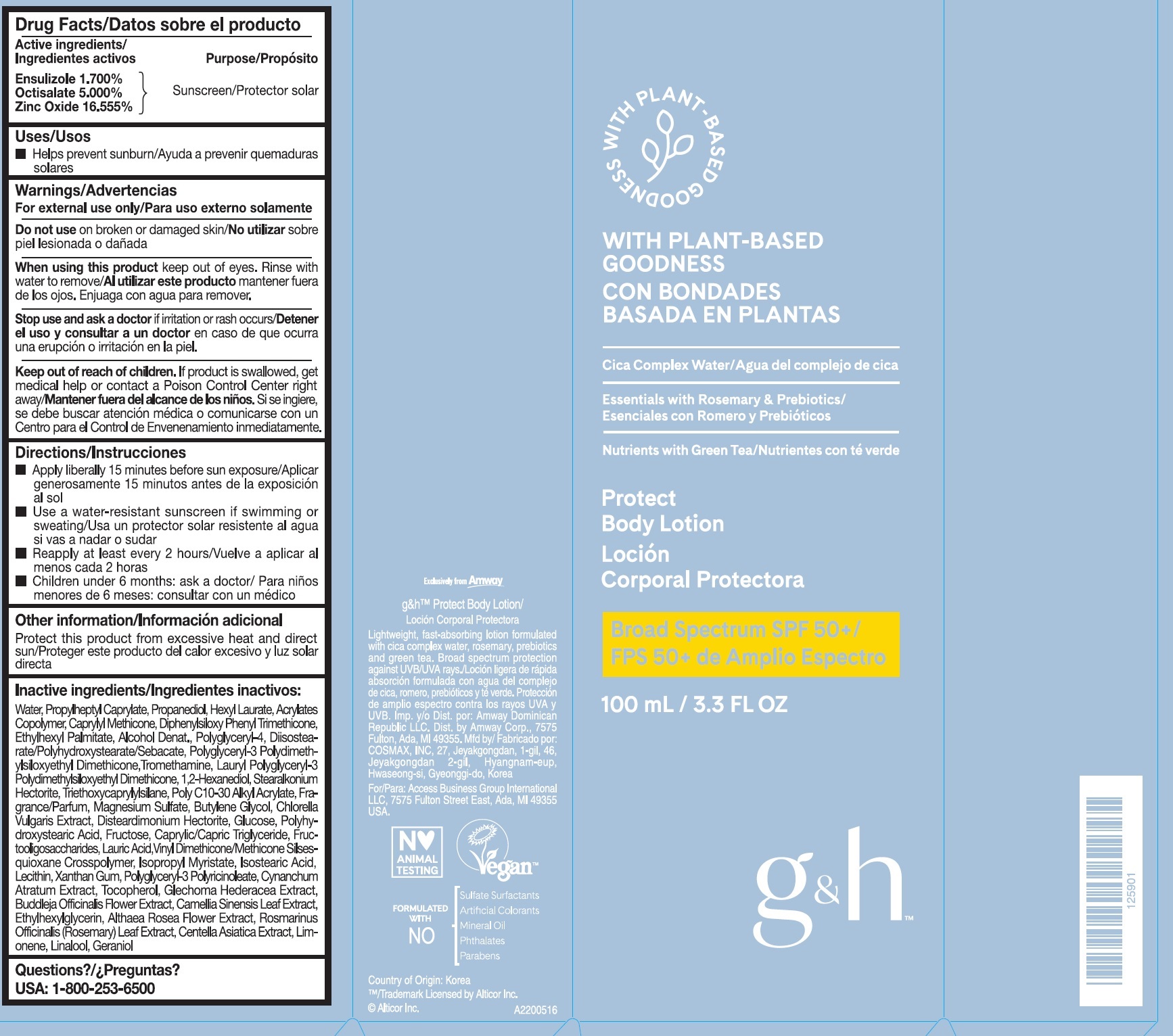 DRUG LABEL: g and h Protect Body
NDC: 10056-025 | Form: LOTION
Manufacturer: Access Business Group LLC
Category: otc | Type: HUMAN OTC DRUG LABEL
Date: 20231023

ACTIVE INGREDIENTS: ENSULIZOLE 17 mg/1 mL; OCTISALATE 50 mg/1 mL; ZINC OXIDE 165.55 mg/1 mL
INACTIVE INGREDIENTS: WATER; PROPYLHEPTYL CAPRYLATE; PROPANEDIOL; HEXYL LAURATE; CAPRYLYL TRISILOXANE; DIPHENYLSILOXY PHENYL TRIMETHICONE; ETHYLHEXYL PALMITATE; ALCOHOL; TROMETHAMINE; 1,2-HEXANEDIOL; STEARALKONIUM HECTORITE; TRIETHOXYCAPRYLYLSILANE; MAGNESIUM SULFATE, UNSPECIFIED FORM; BUTYLENE GLYCOL; CHLORELLA VULGARIS; DISTEARDIMONIUM HECTORITE; ANHYDROUS DEXTROSE; FRUCTOSE; MEDIUM-CHAIN TRIGLYCERIDES; LAURIC ACID; VINYL DIMETHICONE/METHICONE SILSESQUIOXANE CROSSPOLYMER; ISOPROPYL MYRISTATE; ISOSTEARIC ACID; XANTHAN GUM; TOCOPHEROL; GLECHOMA HEDERACEA WHOLE; GREEN TEA LEAF; ETHYLHEXYLGLYCERIN; ALCEA ROSEA FLOWER; ROSEMARY; CENTELLA ASIATICA TRITERPENOIDS; LIMONENE, (+)-; LINALOOL, (+/-)-; GERANIOL

g&h Protect Body Lotion

Active ingredients

Ensulizole 1.700%

Octisalate 5.000%

Zinc Oxide 16.555%

Purpose

Sunscreen

Uses

- Helps prevent sunburn

Warnings

For external use only

Do not use

on broken or damaged skin

When using this product

kep out of eyes. Rinse with water to remove

Stop use and ask a doctor

if irritation or rash occurs

Keep out of reach of children.

If product is swallowed, get medical help or contact a Poison Control Center right away

Directions

- Apply liberally 15 minutes before sun exposure
- Use a water-resistant sunscreen if swimming or sweating
- Reapply at least every 2 hours
- Children under 6 months: ask a doctor

Other information

Protect this product from excessive heat and direct sun

Inactive ingredients

Water, Propylheptyl Caprylate, Propanediol, Hexyl Laurate, Acrylates Copolymer, Caprylyl Methicone, Diphenylsiloxy Phenyl Trimethicone, Ethylhexyl Palmitate, Alcohol Denat., Polyglyceryl-4, Diisostearate/Polyhydroxystearate/Sebacate, Polyglyceryl-3 Polydimethylsiloxyethyl Dimethicone, Tromethamine, Lauryl Polyglyceryl-3 Polydimethylsiloxyethyl Dimethicone, 1,2-Hexanediol, Stearalkonium Hectorite, Triethoxycaprylylsilane, Poly C10-30 Alkyl Acrylate, Fragrance/Parfum, Magnesium Sulfate, Butylene Glycol, Chlorella Vulgaris Extract, Disteardimonium Hectorite, Glucose, Polyhydorxystearic Acid, Fructose, Caprylic/Capric Triglyceride, Fructooligosaccharides, Lauric Acid, Vinyl Dimethicone/Methicone Silsesquioxane Crosspolymer, Isopropyl Myristate, Isostearic Acid, Lecithin, Xanthan Gum, Polyglyceryl-3 Polyricinoleate, Cynanchum Atratum Extract, Tocopherol, Glechoma Hederacea Extract, Buddleja Officinalis Flower Extract, Camellia Sinensis Leaf Extract, Ethylhexylglycerin, Althaea Rosea Flower Extract, Rosmarinus Officinalis (Rosemary) Leaf Extract, Centella Asiatica Extract, Limonene, Linalool, Geraniol

Question?

USA: 1-800-253-6500